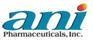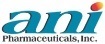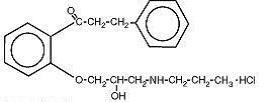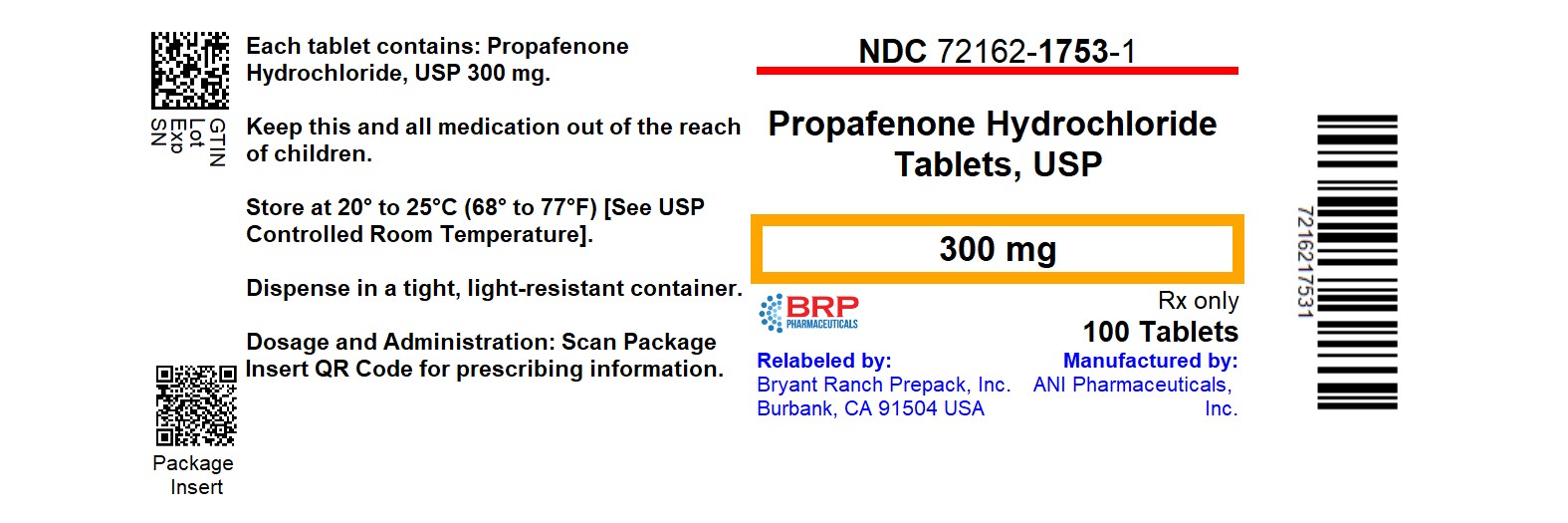 DRUG LABEL: Propafenone Hydrochloride
NDC: 72162-1753 | Form: TABLET, COATED
Manufacturer: Bryant Ranch Prepack
Category: prescription | Type: HUMAN PRESCRIPTION DRUG LABEL
Date: 20260226

ACTIVE INGREDIENTS: PROPAFENONE HYDROCHLORIDE 300 mg/1 1
INACTIVE INGREDIENTS: STARCH, CORN; POVIDONE K30; CROSCARMELLOSE SODIUM; MICROCRYSTALLINE CELLULOSE; SILICON DIOXIDE; MAGNESIUM STEARATE; HYPROMELLOSE, UNSPECIFIED; MALTODEXTRIN; POLYETHYLENE GLYCOL, UNSPECIFIED; TITANIUM DIOXIDE; POLYDEXTROSE; TRIACETIN

HIGHLIGHTS OF PRESCRIBING INFORMATION

These highlights do not include all the information needed to use PROPAFENONE HYDROCHLORIDE TABLETSsafely and effectively. See full prescribing information for PROPAFENONE HYDROCHLORIDE TABLETS.
PROPAFENONE HYDROCHLORIDE tablets, for oral use
Initial U.S. Approval: 1989

WARNING: MORTALITY

See full prescribing information for complete boxed warning.

- An increased rate of death or reversed cardiac arrest rate was seen in subjects treated with encainide or flecainide (Class IC antiarrhythmics) compared with that seen in patients assigned to placebo. At present, it is prudent to consider any IC antiarrhythmic to have a significant risk of provoking proarrhythmic events in subjects with structural heart disease.
- Given the lack of any evidence that these drugs improve survival, antiarrhythmic agents should generally be avoided in patients with non-life-threatening ventricular arrhythmias, even if the patients are experiencing unpleasant, but not life-threatening, symptoms or signs.

1 INDICATIONS AND USAGE

Propafenone Hydrochloride Tablets are an antiarrhythmic indicated to:

- prolong the time to recurrence of symptomatic atrial fibrillation (AF) in patients with episodic (most likely paroxysmal or persistent) AF who do not have structural heart disease. (1)
- prolong the time to recurrence of paroxysmal supraventricular tachycardia (PSVT) associated with disabling symptoms in patients who do not have structural heart disease. (1)
- treat documented life-threatening ventricular arrhythmias. (1)

Usage Considerations:

- Use in patients with permanent atrial fibrillation or with atrial flutter or PSVT has not been evaluated. Do not use to control ventricular rate during atrial fibrillation. (1)
- In patients with atrial fibrillation and atrial flutter, use Propafenone Hydrochloride Tablets with drugs that increase the atrioventricular nodal refractory period. (1)
- Because of proarrhythmic effects, use with lesser ventricular arrhythmias is not recommended, even if patients are symptomatic. (1)
- The effect of propafenone on mortality has not been determined. (1)

2 DOSAGE AND ADMINISTRATION

- Initiate therapy with 150 mg given every 8 hours. (2)
- As needed, uptitrate in 3 to 4 days to 225 to 300 mg every 8 hours. (2)
- Consider reducing the dose in patients with hepatic impairment, significant widening of the QRS complex, or second- or third-degree AV block. (2)

3 DOSAGE FORMS AND STRENGTHS

Tablets: 150 mg, 225 mg, 300 mg.

4 CONTRAINDICATIONS

- Heart failure (4)
- Cardiogenic shock (4)
- Sinoatrial, atrioventricular, and intraventricular disorders of impulse generation or conduction in the absence of pacemaker (4)
- Known Brugada Syndrome (4)
- Bradycardia (4)
- Marked hypotension (4)
- Bronchospastic disorders and severe obstructive pulmonary disease (4)
- Marked electrolyte imbalance (4)

5 WARNINGS AND PRECAUTIONS

- May cause new or worsened arrhythmias. Evaluate patients via ECG prior to and during therapy. (5.1)
- Propafenone Hydrochloride Tablets may unmask Brugada or Brugada-like Syndrome. (4, 5.2)
- Avoid use with other drugs that prolong the QT interval. (5.3)
- Avoid simultaneous use of propafenone with both a cytochrome P450 2D6 (CYP2D6) inhibitor and a 3A4 inhibitor (CYP3A4). (5.4)
- May provoke overt heart failure. (5.5)
- May cause dose-related first-degree AV block or other conduction disturbances. Only use in patients with conduction disorders who have pacemakers. (5.6)
- May affect artificial pacemakers. Monitor pacemaker function. (5.7)
- Agranulocytosis: Patients should report signs of infection. (5.8)
- May exacerbate myasthenia gravis. (5.11)

6 ADVERSE REACTIONS

The most commonly reported adverse events with propafenone (greater than 5%) included: unusual taste, nausea and/or vomiting, dizziness, constipation, headache, fatigue, first-degree AV block, and intraventricular conduction delay. (6.1)

To report SUSPECTED ADVERSE REACTIONS, contact ANI Pharmaceuticals, Inc. at 1-800-308-6755 or FDA at 1-800-FDA-1088 or www.fda.gov/medwatch.

7 DRUG INTERACTIONS

- Inhibitors of CYP2D6, 1A2, and 3A4 increase propafenone exposure. (7.1)
- Propafenone may increase digoxin or warfarin levels. (7.2, 7.3)
- Orlistat may reduce propafenone exposure. Taper orlistat withdrawal. (7.4)
- Lidocaine may increase central nervous system side effects. (7.6)

FULL PRESCRIBING INFORMATION

WARNING: MORTALITY

- In the National Heart, Lung, and Blood Institute’s Cardiac Arrhythmia Suppression Trial (CAST), a long-term, multicenter, randomized, double-blind trial in subjects with asymptomatic non-life-threatening ventricular arrhythmias who had a myocardial infarction more than 6 days but less than 2 years previously, an increased rate of death or reversed cardiac arrest rate (7.7%; 56/730) was seen in subjects treated with encainide or flecainide (Class IC antiarrhythmics) compared with that seen in subjects assigned to placebo (3.0%; 22/725). The average duration of treatment with encainide or flecainide in this trial was 10 months.
- The applicability of the CAST results to other populations (e.g., those without recent myocardial infarction) or other antiarrhythmic drugs is uncertain, but at present, it is prudent to consider any IC antiarrhythmic to have a significant proarrhythmic risk in patients with structural heart disease. Given the lack of any evidence that these drugs improve survival, antiarrhythmic agents should generally be avoided in patients with non-life-threatening ventricular arrhythmias, even if the patients are experiencing unpleasant, but not life-threatening, symptoms or signs.

1 INDICATIONS AND USAGE

Propafenone Hydrochloride Tablets are indicated to:

- prolong the time to recurrence of paroxysmal atrial fibrillation/flutter (PAF) associated with disabling symptoms in patients without structural heart disease.
- prolong the time to recurrence of paroxysmal supraventricular tachycardia (PSVT) associated with disabling symptoms in patients without structural heart disease.
- treat documented ventricular arrhythmias, such as sustainedventricular tachycardia that, in the judgment of the physician, are life-threatening. Initiate treatment in the hospital.

Usage Considerations:

- The use of Propafenone Hydrochloride Tablets in patients with permanent atrial fibrillation (AF) or in patients exclusively with atrial flutter or PSVT has not been evaluated. Do not use Propafenone Hydrochloride Tablets to control ventricular rate during AF.
- Some patients with atrial flutter treated with propafenone have developed 1:1 conduction, producing an increase in ventricular rate. Concomitant treatment with drugs that increase the functional atrioventricular (AV) nodal refractory period is recommended.
- The use of Propafenone Hydrochloride Tablets in patients with chronic atrial fibrillation has not been evaluated.
- Because of the proarrhythmic effects of Propafenone Hydrochloride Tablets, its use with lesser ventricular arrhythmias is not recommended, even if patients are symptomatic, and any use of the drug should be reserved for patients in whom, in the opinion of the physician, the potential benefits outweigh the risks.
- The effect of propafenone on mortality has not been determined [see Boxed Warning] .

2 DOSAGE AND ADMINISTRATION

The dose of Propafenone Hydrochloride Tablets must be individually titrated on the basis of response and tolerance. Initiate therapy with Propafenone Hydrochloride Tablets 150 mg given every 8 hours (450 mg per day). Dosage may be increased at a minimum of 3- to 4- day intervals to 225 mg every 8 hours (675 mg per day). If additional therapeutic effect is needed, the dose of Propafenone Hydrochloride Tablets may be increased to 300 mg every 8 hours (900 mg per day). The usefulness and safety of dosages exceeding 900 mg per day have not been established.

In patients with hepatic impairment or those with significant widening of the QRS complex or second- or third-degree AV block, consider reducing the dose.

As with other antiarrhythmic agents, in the elderly or in ventricular arrhythmia patients with marked previous myocardial damage, the dose of Propafenone Hydrochloride Tablets should be increased more gradually during the initial phase of treatment.

The combination of cytochrome P450 3A4 (CYP3A4) inhibition and either cytochrome P450 2D6 (CYP2D6) deficiency or CYP2D6 inhibition with the simultaneous administration of propafenone may significantly increase the concentration of propafenone and thereby increase the risk of proarrhythmia and other adverse events. Therefore, avoid simultaneous use of Propafenone Hydrochloride Tablets with both a CYP2D6 inhibitor and a CYP3A4 inhibitor [see Warnings and Precautions (5.4), Drug Interactions (7.1)] .

3 DOSAGE FORMS AND STRENGTHS

150 mg, 225 mg, and 300 mg scored, round, film-coated tablets.

4 CONTRAINDICATIONS

Propafenone hydrochloride tablets are contraindicated in the following circumstances:

- Heart failure
- Cardiogenic shock
- Sinoatrial, atrioventricular, and intraventricular disorders of impulse generation or conduction (e.g., sick sinus node syndrome, AV block) in the absence of an artificial pacemaker
- Known Brugada Syndrome
- Bradycardia
- Marked hypotension
- Bronchospastic disorders or severe obstructive pulmonary disease
- Marked electrolyte imbalance

5 WARNINGS AND PRECAUTIONS

5.1 Proarrhythmic Effects

Propafenone has caused new or worsened arrhythmias. Such proarrhythmic effects include sudden death and life-threatening ventricular arrhythmias such as ventricular fibrillation, ventricular tachycardia, asystole, and torsade de pointes. It may also worsen premature ventricular contractions or supraventricular arrhythmias, and it may prolong the QT interval. It is therefore essential that each patient given propafenone hydrochloride tablets be evaluated electrocardiographically prior to and during therapy to determine whether the response to propafenone hydrochloride tablets supports continued treatment. Because propafenone prolongs the QRS interval in the electrocardiogram, changes in the QT interval are difficult to interpret [see Clinical Pharmacology (12.2)].

In a U.S. uncontrolled, open-label, multicenter trial in subjects with symptomatic supraventricular tachycardia (SVT), 1.9% (9/474) of these subjects experienced ventricular tachycardia (VT) or ventricular fibrillation (VF) during the trial. However, in 4 of the 9 subjects, the ventricular tachycardia was of atrial origin. Six of the 9 subjects that developed ventricular arrhythmias did so within 14 days of onset of therapy. About 2.3% (11/474) of all subjects had a recurrence of SVT during the trial which could have been a change in the subjects’ arrhythmia behavior or could represent a proarrhythmic event. Case reports in patients treated with propafenone for atrial fibrillation/flutter have included increased premature ventricular contractions (PVCs), VT, VF, torsade de pointes, asystole, and death.

Overall in clinical trials with propafenone hydrochloride tablets (which included subjects treated for ventricular arrhythmias, atrial fibrillation/flutter, and PSVT), 4.7% of all subjects had new or worsened ventricular arrhythmia possibly representing a proarrhythmic event (0.7% was an increase in PVCs; 4.0% a worsening or new appearance of VT or VF). Of the subjects who had worsening of VT (4%), 92% had a history of VT and/or VT/VF, 71% had coronary artery disease, and 68% had a prior myocardial infarction. The incidence of proarrhythmia in subjects with less serious or benign arrhythmias, which include subjects with an increase in frequency of PVCs, was 1.6%. Although most proarrhythmic events occurred during the first week of therapy, late events also were seen and the CAST trial [see Boxed Warning: Mortality] suggests that an increased risk of proarrythmia is present throughout treatment.

In a trial of sustained-release propafenone, there were too few deaths to assess the long-term risk to patients. There were 5 deaths; 3 in the pooled group for sustained-release propafenone (0.8%), and 2 in the placebo group (1.6%). In the overall database of 8 trials of sustained-release propafenone and immediate-release propafenone, the mortality rate was 2.5% per year on propafenone and 4.0% per year on placebo. Concurrent use of propafenone with other antiarrhythmic agents has not been well studied.

5.2 Unmasking Brugada Syndrome

Brugada Syndrome may be unmasked after exposure to propafenone hydrochloride tablets. Perform an ECG after initiation of propafenone hydrochloride tablets, and discontinue the drug if changes are suggestive of Brugada Syndrome [see Contraindications (4)] .

5.3 Use with Drugs that Prolong the QT Interval and Antiarrhythmic Agents

The use of propafenone hydrochloride tablets in conjunction with other drugs that prolong the QT interval has not been extensively studied. Such drugs may include many antiarrhythmics, some phenothiazines, tricyclic antidepressants, and oral macrolides. Withhold Class IA and III antiarrhythmic agents for at least 5 half-lives prior to dosing with propafenone hydrochloride tablets. Avoid the use of propafenone with Class IA and III antiarrhythmic agents (including quinidine and amiodarone). There is only limited experience with the concomitant use of Class IB or IC antiarrhythmics.

5.4 Drug Interactions: Simultaneous Use with Inhibitors of Cytochrome P450 Isoenzymes 2D6 and 3A4

Propafenone is metabolized by CYP2D6, CYP3A4, and CYP1A2 isoenzymes. Approximately 6% of Caucasians in the U.S. population are naturally deficient in CYP2D6 activity and other demographic groups are deficient to a somewhat lesser extent. Drugs that inhibit these CYP pathways (such as desipramine, paroxetine, ritonavir, sertraline for CYP2D6; ketoconazole, erythromycin, saquinavir, and grapefruit juice for CYP3A4; and amiodarone and tobacco smoke for CYP1A2) can be expected to cause increased plasma levels of propafenone.

Increased exposure to propafenone may lead to cardiac arrhythmias and exaggerated beta-adrenergic blocking activity. Because of its metabolism, the combination of CYP3A4 inhibition and either CYP2D6 deficiency or CYP2D6 inhibition in users of propafenone is potentially hazardous. Therefore, avoid simultaneous use of propafenone hydrochloride tablets with both a CYP2D6 inhibitor and a CYP3A4 inhibitor.

5.5 Use in Patients with a History of Heart Failure

Propafenone exerts a negative inotropic activity on the myocardium as well as beta-blockade effects and may provoke overt heart failure.

In clinical trial experience with propafenone hydrochloride tablets, new or worsened congestive heart failure (CHF) has been reported in 3.7% of subjects with ventricular arrhythmia; of those 0.9% were considered probably or definitely related to propafenone hydrochloride. Of the subjects with CHF probably related to propafenone, 80% had pre-existing heart failure and 85% had coronary artery disease. CHF attributable to propafenone hydrochloride developed rarely (less than 0.2%) in subjects with ventricular arrhythmia who had no previous history of CHF. CHF occurred in 1.9% of subjects studied with PAF or PSVT.

In a U.S. trial of sustained-release propafenone in subjects with symptomatic AF, heart failure was reported in 4 (1.0%) subjects receiving sustained-release propafenone (all doses) compared to 1 (0.8%) subject receiving placebo.

5.6 Conduction Disturbances

Propafenone slows atrioventricular conduction and may also cause dose-related first degree AV block. Average PR interval prolongation and increases in QRS duration are also dose-related. Do not give propafenone to patients with atrioventricular and intraventricular conduction defects in the absence of a pacemaker [see Contraindications (4), Clinical Pharmacology (12.2)] .

The incidence of first-degree, second-degree, and third-degree AV block observed in 2,127 subjects with ventricular arrhythmia was 2.5%, 0.6%, and 0.2%, respectively. Development of second- or third-degree AV block requires a reduction in dosage or discontinuation of propafenone hydrochloride. Bundle branch block (1.2%) and intraventricular conduction delay (1.1%) have been reported in subjects receiving propafenone. Bradycardia has also been reported (1.5%). Experience in patients with sick sinus node syndrome is limited and these patients should not be treated with propafenone.

In a U.S. trial in 523 subjects with a history of symptomatic AF treated with sustained-release propafenone, sinus bradycardia (rate less than 50 beats/min) was reported with the same frequency with sustained-release propafenone and placebo.

5.7 Effects on Pacemaker Threshold

Propafenone may alter both pacing and sensing thresholds of implanted pacemakers and defibrillators. During and after therapy, monitor and re-program these devices accordingly.

5.8 Agranulocytosis

Agranulocytosis has been reported in patients receiving propafenone. Generally, the agranulocytosis occurred within the first 2 months of propafenone therapy, and upon discontinuation of therapy the white count usually normalized by 14 days. Unexplained fever or decrease in white cell count, particularly during the initial 3 months of therapy, warrant consideration of possible agranulocytosis or granulocytopenia. Instruct patients to report promptly any signs of infection such as fever, sore throat, or chills.

5.9 Use in Patients with Hepatic Dysfunction

Propafenone is highly metabolized by the liver. Severe liver dysfunction increases the bioavailability of propafenone to approximately 70% compared with 3% to 40% in patients with normal liver function. In 8 subjects with moderate to severe liver disease, the mean half-life was approximately 9 hours. Increased bioavailability of propafenone in these patients may result in excessive accumulation. Carefully monitor patients with impaired hepatic function for excessive pharmacological effects [see Overdosage (10)] .

5.10 Use in Patients with Renal Dysfunction

Approximately 50% of propafenone metabolites are excreted in the urine following administration of propafenone hydrochloride tablets.

In patients with impaired renal function, monitor for signs of overdosage [see Overdosage (10)] .

5.11 Use in Patients with Myasthenia Gravis

Exacerbation of myasthenia gravis has been reported during propafenone therapy.

5.12 Elevated ANA Titers

Positive ANA titers have been reported in patients receiving propafenone. They have been reversible upon cessation of treatment and may disappear even in the face of continued propafenone therapy. These laboratory findings were usually not associated with clinical symptoms, but there is one published case of drug-induced lupus erythematosis (positive rechallenge); it resolved completely upon discontinuation of therapy. Carefully evaluate patients who develop an abnormal ANA test and, if persistent or worsening elevation of ANA titers is detected, consider discontinuing therapy.

6 ADVERSE REACTIONS

6.1 Clinical Trials Experience

Because clinical trials are conducted under widely varying conditions, adverse reaction rates observed in the clinical trials of a drug cannot be directly compared with rates in the clinical trials of another drug and may not reflect the rates observed in practice.

Adverse reactions associated with propafenone hydrochloride tablets occur most frequently in the gastrointestinal, cardiovascular, and central nervous systems. About 20% of subjects treated with propafenone hydrochloride tablets have discontinued treatment because of adverse reactions.

Adverse reactions reported for greater than 1.5% of 474 subjects with SVT who received propafenone hydrochloride tablets in U.S. clinical trials are presented in Table 1 by incidence and percent discontinuation, reported to the nearest percent.

Table 1. Adverse Reactions Reported for >1.5% of Subjects with Supraventricular Tachycardia

Adverse Reaction | Incidence; (n = 480) | % of Subjects Who Discontinued
Unusual taste | 14% | 1.3%
Nausea and/or vomiting | 11% | 2.9%
Dizziness | 9% | 1.7%
Constipation | 8% | 0.2%
Headache | 6% | 0.8%
Fatigue | 6% | 1.5%
Blurred vision | 3% | 0.6%
Weakness | 3% | 1.3%
Dyspnea | 2% | 1.0%
Wide complex tachycardia | 2% | 1.9%
CHF | 2% | 0.6%
Bradycardia | 2% | 0.2%
Palpitations | 2% | 0.2%
Tremor | 2% | 0.4%
Anorexia | 2% | 0.2%
Diarrhea | 2% | 0.4%
Ataxia | 2% | 0.0%

In controlled trials in subjects with ventricular arrhythmia, the most common reactions reported for propafenone hydrochloride tablets and more frequent than on placebo were unusual taste, dizziness, first-degree AV block, intraventricular conduction delay, nausea and/or vomiting, and constipation. Headache was relatively common also, but was not increased compared with placebo. Other reactions reported more frequently than on placebo or comparator and not already reported elsewhere included anxiety, angina, second-degree AV block, bundle branch block, loss of balance, congestive heart failure, and dyspepsia.

Adverse reactions reported for greater than or equal to 1% of 2,127 subjects with ventricular arrhythmia who received propafenone in U.S. clinical trials were evaluated by daily dose. The most common adverse reactions appeared dose-related (but note that most subjects spent more time at the larger doses), especially dizziness, nausea and/or vomiting, unusual taste, constipation, and blurred vision. Some less common reactions may also have been dose-related such as first-degree AV block, congestive heart failure, dyspepsia, and weakness. Other adverse reactions included rash, syncope, chest pain, abdominal pain, ataxia, and hypotension.

In addition, the following adverse reactions were reported less frequently than 1% either in clinical trials or in marketing experience. Causality and relationship to propafenone therapy cannot necessarily be judged from these events.

Cardiovascular System
Atrial flutter, AV dissociation, cardiac arrest, flushing, hot flashes, sick sinus syndrome, sinus pause or arrest, supraventricular tachycardia.

Nervous System
Abnormal dreams, abnormal speech, abnormal vision, confusion, depression, memory loss, numbness, paresthesias, psychosis/mania, seizures (0.3%), tinnitus, unusual smell sensation, vertigo.

Gastrointestinal
Cholestasis, elevated liver enzymes (alkaline phosphatase, serum transaminases), gastroenteritis, hepatitis.

Hematologic
Agranulocytosis, anemia, bruising, granulocytopenia, leukopenia, purpura, thrombocytopenia.

Other
Alopecia, eye irritation, impotence, increased glucose, positive ANA (0.7%), muscle cramps, muscle weakness, nephrotic syndrome, pain, pruritus.

6.2 Postmarketing Experience

The following adverse reactions have been identified during post-approval use of propafenone hydrochloride tablets. Because these reactions are reported voluntarily from a population of uncertain size, it is not always possible to reliably estimate their frequency or establish a causal relationship to drug exposure.

Gastrointestinal
A number of patients with liver abnormalities associated with propafenone therapy have been reported in postmarketing experience. Some appeared due to hepatocellular injury, some were cholestatic, and some showed a mixed picture. Some of these reports were simply discovered through clinical chemistries, others because of clinical symptoms including fulminant hepatitis and death. One case was rechallenged with a positive outcome.

Blood and Lymphatic System
Increased bleeding time.

Immune System
Lupus erythematosis.

Nervous System
Apnea, coma.

Renal and Urinary
Hyponatremia/inappropriate ADH secretion, kidney failure.

7 DRUG INTERACTIONS

7.1 CYP2D6 and CYP3A4 Inhibitors

Drugs that inhibit CYP2D6 (such as desipramine, paroxetine, ritonavir, sertraline) and CYP3A4 (such as ketoconazole, ritonavir, saquinavir, erythromycin, grapefruit juice) can be expected to cause increased plasma levels of propafenone. The combination of CYP3A4 inhibition and either CYP2D6 deficiency or CYP2D6 inhibition with administration of propafenone may increase the risk of adverse reactions, including proarrhythmia. Therefore, simultaneous use of propafenone hydrochloride tablets with both a CYP2D6 inhibitor and a CYP3A4 inhibitor should be avoided [see Warnings and Precautions (5.4), Dosage and Administration (2)] .

Amiodarone
Concomitant administration of propafenone and amiodarone can affect conduction and repolarization and is not recommended.

Cimetidine
Concomitant administration of propafenone immediate-release tablets and cimetidine in 12 healthy subjects resulted in a 20% increase in steady-state plasma concentrations of propafenone.

Fluoxetine
Concomitant administration of propafenone and fluoxetine in extensive metabolizers increased the S-propafenone Cmaxand AUC by 39% and 50%, respectively, and the R-propafenone Cmaxand AUC by 71% and 50%, respectively.

Quinidine
Small doses of quinidine completely inhibit the CYP2D6 hydroxylation metabolic pathway, making all patients, in effect, slow metabolizers [see Clinical Pharmacology (12.3)]. Concomitant administration of quinidine (50 mg 3 times daily) with 150 mg immediate-release propafenone 3 times daily decreased the clearance of propafenone by 60% in extensive metabolizers, making them slow metabolizers. Steady-state plasma concentrations more than doubled for propafenone and decreased 50% for 5-OH-propafenone. A 100-mg dose of quinidine tripled steady-state concentrations of propafenone. Avoid concomitant use of propafenone and quinidine.

Rifampin
Concomitant administration of rifampin and propafenone in extensive metabolizers decreased the plasma concentrations of propafenone by 67% with a corresponding decrease of 5-OH-propafenone by 65%. The concentrations of norpropafenone increased by 30%. In slow metabolizers, there was a 50% decrease in propafenone plasma concentrations and an increase in the AUC and Cmaxof norpropafenone by 74% and 20%, respectively. Urinary excretion of propafenone and its metabolites decreased significantly. Similar results were noted in elderly patients: Both the AUC and Cmaxof propafenone decreased by 84%, with a corresponding decrease in AUC and Cmaxof 5-OH-propafenone by 69% and 57%, respectively.

7.2 Digoxin

Concomitant use of propafenone and digoxin increased steady-state serum digoxin exposure (AUC) in patients by 60% to 270% and decreased the clearance of digoxin by 31% to 67%. Monitor plasma digoxin levels of patients receiving propafenone and adjust digoxin dosage as needed.

7.3 Warfarin

The concomitant administration of propafenone and warfarin increased warfarin plasma concentrations at steady state by 39% in healthy volunteers and prolonged the prothrombin time (PT) in patients taking warfarin. Adjust the warfarin dose as needed by monitoring INR (international normalized ratio).

7.4 Orlistat

Orlistat may limit the fraction of propafenone available for absorption. In postmarketing reports, abrupt cessation of orlistat in patients stabilized on propafenone has resulted in severe adverse events including convulsions, atrioventricular block, and acute circulatory failure.

7.5 Beta-Antagonists

Concomitant use of propafenone and propranolol in healthy subjects increased propranolol plasma concentrations at steady state by 113%. In 4 patients, administration of metoprolol with propafenone increased the metoprolol plasma concentrations at steady state by 100% to 400%. The pharmacokinetics of propafenone was not affected by the coadministration of either propranolol or metoprolol. In clinical trials using propafenone immediate-release tablets, subjects who were receiving beta-blockers concurrently did not experience an increased incidence of side effects.

7.6 Lidocaine

No significant effects on the pharmacokinetics of propafenone or lidocaine have been seen following their concomitant use in patients. However, concomitant use of propafenone and lidocaine has been reported to increase the risks of central nervous system side effects of lidocaine.

8 USE IN SPECIFIC POPULATIONS

8.1 Pregnancy

Risk Summary
There are no studies of propafenone hydrochloride tablets in pregnant women. Available data from published case reports and several decades of postmarketing experience with use of propafenone hydrochloride tablets in pregnancy have not identified any drug-associated risks of miscarriage, birth defects, or adverse maternal or fetal outcomes. Untreated arrhythmias during pregnancy may pose a risk to the pregnant woman and fetus (see Clinical Considerations). Propafenone and its metabolite, 5-OH-propafenone, cross the placenta in humans. In animal studies, propafenone was not teratogenic. At maternally toxic doses (ranging from 2 to 6 times the maximum recommended human dose [MRHD]), there was evidence of adverse developmental outcomes when administered to pregnant rabbits and rats during organogenesis or when administered to pregnant rats during mid-gestation through weaning of their offspring (see Data).

The estimated background risks of major birth defects and miscarriage for the indicated populations are unknown. All pregnancies have a background risk of birth defect, loss, or other adverse outcomes. In the U.S. general population, the estimated background risk of major birth defects and miscarriage in clinically recognized pregnancies is 2% to 4% and 15% to 20%, respectively.

Clinical Considerations
Disease-associated maternal and/or embryo/fetal risk:The incidence of VT is increased and may be more symptomatic during pregnancy. Ventricular arrhythmias most often occur in pregnant women with underlying cardiomyopathy, congenital heart disease, valvular heart disease, or mitral valve prolapse. Breakthrough arrhythmias may also occur during pregnancy, as therapeutic treatment levels may be difficult to maintain due to the increased volume of distribution and increased drug metabolism inherent in the pregnant state.

Fetal/Neonatal Adverse Reactions:Propafenone and its metabolite have been shown to cross the placenta. Adverse reactions such as fetal/neonatal arrhythmias have been associated with the use of other antiarrhythmic agents by pregnant women. Fetal/neonatal monitoring for signs and symptoms of arrhythmia is recommended during and after treatment of pregnant women with propafenone.

Labor or Delivery:Risk of arrhythmias may increase during labor and delivery. Patients treated with propafenone hydrochloride tablets should be monitored continuously for arrhythmias during labor and delivery [see Warnings and Precautions (5.1)] .

Data
Propafenone has been shown to cause embryo-fetal mortality in rabbits and rats when given orally during organogenesis at maternally toxic doses of 150 mg/kg/day (rabbit: maternal mortality, decreased body weight gain and food consumption at approximately 3 times the MRHD on a mg/m^2basis) and 600 mg/kg/day (rat: maternal decreased body weight gain and food consumption at approximately 6 times the MRHD on a mg/m^2basis). In addition, a maternally toxic dose of 600 mg/kg/day (approximately 6 times the MRHD on a mg/m^2basis) also caused decreased fetal weights in rats. Increased placental weights and delayed ossification occurred in rabbits at a dose of 30 mg/kg/day (less than the MRHD on a mg/m^2basis) in the absence of maternal toxicity. No adverse developmental outcomes in the absence of maternal toxicity were seen following oral doses of 15 mg/kg/day to rabbits or up to 270 mg/kg/day to rats administered during organogenesis (equivalent to 0.3 times or approximately 3 times the MRHD on a mg/m^2basis, respectively). In an oral study, female rats received propafenone up to 500 mg/kg/day from mid-gestation through weaning. At 90 mg/kg/day (equivalent to the MRHD on a mg/m^2basis), there were no adverse developmental outcomes in the absence of maternal toxicity. However, doses ≥180 mg/kg/day (2 or more times the MRHD on a mg/m^2basis) produced increases in maternal deaths and resulted in reductions in neonatal survival, body weight gain, and delayed development in the presence of maternal toxicity.

8.2 Lactation

Risk Summary
Propafenone and its active metabolite, 5-OH-propafenone, are present in human milk, but the levels are likely to be low. There are no data on the effects of propafenone on the breastfed infant or the effects on milk production.

The developmental and health benefits of breastfeeding should be considered along with the mother’s clinical need for propafenone and any potential adverse effects on the breastfed infant from propafenone or from the underlying maternal condition.

8.3 Females and Males of Reproductive Potential

Infertility
Males:Based on human and animal studies, propafenone hydrochloride tablets may transiently impair spermatogenesis in males. Evaluation of the effects on spermatogenesis was performed in 11 healthy males given oral propafenone 300 mg b.i.d. for 4 days, which was then increased to 300 mg t.i.d. for an additional 4 days. Study findings included a 28% reduction in semen sample volume on Treatment Day 8 and a 27% reduction in sperm count 64 days after treatment (both values remained within the laboratories normal reference range). These effects were not seen in follow-up visits up to 120 days after treatment. Reversible decreases in spermatogenesis have been demonstrated in monkeys, dogs, and rabbits after lethal or near-lethal intravenous doses of propafenone [see Nonclinical Toxicology (13.1)] .

8.4 Pediatric Use

The safety and effectiveness of propafenone in pediatric patients have not been established.

8.5 Geriatric Use

Clinical trials of propafenone hydrochloride tablets did not include sufficient numbers of subjects aged 65 and older to determine whether they respond differently from younger subjects. Other reported clinical experience has not identified differences in responses between the elderly and younger subjects. In general, dose selection for an elderly patient should be cautious, usually starting at the low end of the dosing range, reflecting the greater frequency of decreased hepatic, renal, or cardiac function, and of concomitant disease or other drug therapy.

10 OVERDOSAGE

The symptoms of overdosage may include hypotension, somnolence, bradycardia, intra-atrial and intraventricular conduction disturbances, and rarely, convulsions and high-grade ventricular arrhythmias. Defibrillation, as well as infusion of dopamine and isoproterenol, has been effective in controlling abnormal rhythm and blood pressure. Convulsions have been alleviated with intravenous diazepam. General supportive measures such as mechanical respiratory assistance and external cardiac massage may be necessary.

The hemodialysis of propafenone in patients with an overdose is expected to be of limited value in the removal of propafenone as a result of both its high protein binding (greater than 95%) and large volume of distribution.

11 DESCRIPTION

Propafenone Hydrochloride Tablets USP are an antiarrhythmic drug supplied in scored, film-coated tablets of 150 mg, 225 mg and 300 mg for oral administration. Propafenone has some structural similarities to beta-blocking agents.

Chemically, propafenone hydrochloride is 2’-[2-hydroxy-3-(propylamino)-propoxy]-3-phenylpropiophenone hydrochloride, with a molecular weight of 377.92. The molecular formula is C21H27NO3•HCl. The structural formula of propafenone hydrochloride is given below:

Propafenone hydrochloride occurs as colorless crystals or white crystalline powder with a very bitter taste. It is slightly soluble in water (20°C), chloroform, and ethanol. The following inactive ingredients are contained in the tablet: corn starch, croscarmellose sodium, hypromellose, maltodextrin, magnesium stearate, microcrystalline cellulose, polydextrose, polyethylene glycol, povidone, silicon dioxide colloidal, titanium dioxide, and triacetin.

12 CLINICAL PHARMACOLOGY

12.1 Mechanism of Action

Propafenone is a Class 1C antiarrhythmic drug with local anesthetic effects and a direct stabilizing action on myocardial membranes. The electrophysiological effect of propafenone manifests itself in a reduction of upstroke velocity (Phase 0) of the monophasic action potential. In Purkinje fibers, and, to a lesser extent, myocardial fibers, propafenone reduces the fast inward current carried by sodium ions. Diastolic excitability threshold is increased and effective refractory period prolonged. Propafenone reduces spontaneous automaticity and depresses triggered activity.

Studies in anesthetized dogs and isolated organ preparations show that propafenone has beta-sympatholytic activity at about 1/50 the potency of propranolol. Clinical studies employing isoproterenol challenge and exercise testing after single doses of propafenone indicate a beta-adrenergic blocking potency (per mg) about 1/40 that of propranolol in man. In clinical trials, resting heart rate decreases of about 8% were noted at the higher end of the therapeutic plasma concentration range. At very high concentrations in vitro, propafenone can inhibit the slow inward current carried by calcium, but this calcium antagonist effect probably does not contribute to antiarrhythmic efficacy. Moreover, propafenone inhibits a variety of cardiac potassium currents in in vitrostudies (i.e., the transient outward, the delayed rectifier, and the inward rectifier current). Propafenone has local anesthetic activity approximately equal to procaine. Compared with propafenone, the main metabolite, 5-hydroxypropafenone, has similar sodium and calcium channel activity, but about 10 times less beta-blocking activity. (N-depropylpropafenone has weaker sodium channel activity but equivalent affinity for beta-receptors.)

12.2 Pharmacodynamics

Cardiac Electrophysiology
Electrophysiology trials in subjects with ventricular tachycardia have shown that propafenone prolongs atrioventricular conduction while having little or no effect on sinus node function. Both atrioventricular nodal conduction time (AH interval) and His-Purkinje conduction time (HV interval) are prolonged. Propafenone has little or no effect on the atrial functional refractory period, but AV nodal functional and effective refractory periods are prolonged. In patients with Wolff-Parkinson-White syndrome, propafenone hydrochloride tablets reduce conduction and increase the effective refractory period of the accessory pathway in both directions.

Electrocardiograms:Propafenone prolongs the PR and QRS intervals. Prolongation of the QRS interval makes it difficult to interpret the effect of propafenone on the QT interval.

Table 2. Mean Changes in Electrocardiogram Intervalsa

Interval | Total Daily Dose (mg)
Interval | 337.5 mg |  | 450 mg |  | 675 mg |  | 900 mg
Interval | msec | % | msec | % | msec | % | msec | %
RR | -14.5 | -1.8 | 30.6 | 3.8 | 31.5 | 3.9 | 41.7 | 5.1
PR | 3.6 | 2.1 | 19.1 | 11.6 | 28.9 | 17.8 | 35.6 | 21.9
QRS | 5.6 | 6.4 | 5.5 | 6.1 | 7.7 | 8.4 | 15.6 | 17.3
QTc | 2.7 | 0.7 | -7.5 | -1.8 | 5.0 | 1.2 | 14.7 | 3.7

a Change and percent change based on mean baseline values for each treatment group.

In any individual patient, the above ECG changes cannot be readily used to predict either efficacy or plasma concentration.

Propafenone hydrochloride tablets cause a dose-related and concentration-related decrease in the rate of single and multiple PVCs and can suppress recurrence of ventricular tachycardia. Based on the percent of patients attaining substantial (80% to 90%) suppression of ventricular ectopic activity, it appears that trough plasma levels of 0.2 to 1.5 mcg/mL can provide good suppression, with higher concentrations giving a greater rate of good response.

When 600 mg/day propafenone was administered to subjects with paroxysmal atrial tachyarrhythmias, mean heart rate during arrhythmia decreased 14 beats per min and 37 beats per min for subjects with PAF and subjects with PSVT, respectively.

Hemodynamics
Trials in humans have shown that propafenone hydrochloride exerts a negative inotropic effect on the myocardium. Cardiac catheterization trials in subjects with moderately impaired ventricular function (mean CI = 2.61 L/min/m^2) utilizing intravenous propafenone infusions (loading dose of 2 mg/kg over 10 min followed by 2 mg/min for 30 min) that gave mean plasma concentrations of 3.0 mcg/mL (a dose that produces plasma levels of propafenone greater than recommended oral dosing) showed significant increases in pulmonary capillary wedge pressure, systemic and pulmonary vascular resistances, and depression of cardiac output and cardiac index.

12.3 Pharmacokinetics

Absorption/Bioavailability
Propafenone hydrochloride is nearly completely absorbed after oral administration with peak plasma levels occurring approximately 3.5 hours after administration in most individuals. Propafenone exhibits extensive saturable presystemic biotransformation (first-pass effect) resulting in a dose-dependent and dosage-form-dependent absolute bioavailability; e.g., a 150-mg tablet had absolute bioavailability of 3.4%, while a 300-mg tablet had absolute bioavailability of 10.6%. A 300-mg solution which was rapidly absorbed had absolute bioavailability of 21.4%. At still larger doses, above those recommended, bioavailability increases still further.

Propafenone hydrochloride follows a nonlinear pharmacokinetic disposition presumably because of saturation of first-pass hepatic metabolism as the liver is exposed to higher concentrations of propafenone and shows a very high degree of inter-individual variability. For example, for an increase in daily dose from 300 to 900 mg/day there is a 10-fold increase in steady-state plasma concentration. The top 25% of subjects given 337.5 mg/day, however, had a mean concentration of propafenone larger than the bottom 25%, and about equal to the second 25%, of subjects given a dose of 900 mg. Although food increased peak blood level and bioavailability in a single-dose trial, during multiple-dose administration of propafenone to healthy volunteers, food did not change bioavailability significantly.

Distribution
Following intravenous administration of propafenone, plasma levels decline in a bi-phasic manner consistent with a 2-compartment pharmacokinetic model. The average distribution half-life corresponding to the first phase was about 5 minutes. The volume of the central compartment was about 88 liters (1.1 L/kg) and the total volume of distribution about 252 liters.

In serum, propafenone is greater than 95% bound to proteins within the concentration range of 0.5 to 2 mcg/mL.

Metabolism
There are 2 genetically determined patterns of propafenone metabolism. In over 90% of patients, the drug is rapidly and extensively metabolized with an elimination half-life from 2 to 10 hours. These patients metabolize propafenone into 2 active metabolites: 5-hydroxypropafenone, which is formed by CYP2D6, and N-depropylpropafenone (norpropafenone), which is formed by both CYP3A4 and CYP1A2.

In less than 10% of patients, metabolism of propafenone is slower because the 5-hydroxy metabolite is not formed or is minimally formed. In these patients, the estimated propafenone elimination half-life ranges from 10 to 32 hours. Decreased ability to form the 5-hydroxy metabolite of propafenone is associated with a diminished ability to metabolize debrisoquine and a variety of other drugs, such as encainide, metoprolol, and dextromethorphan, whose metabolism is mediated by the CYP2D6 isozyme. In these patients, the N-depropylpropafenone metabolite occurs in quantities comparable to the levels occurring in extensive metabolizers.

There are significant differences in plasma concentrations of propafenone in slow and extensive metabolizers, the former achieving concentrations 1.5 to 2.0 times those of the extensive metabolizers at daily doses of 675 to 900 mg/day. At low doses the differences are greater, with slow metabolizers attaining concentrations more than 5 times that of extensive metabolizers. Because the difference decreases at high doses and is mitigated by the lack of the active 5-hydroxy metabolite in the slow metabolizers, and because steady-state conditions are achieved after 4 to 5 days of dosing in all patients, the recommended dosing regimen is the same for all patients. The greater variability in blood levels requires that the drug be titrated carefully in patients with close attention paid to clinical and ECG evidence of toxicity [see Dosage and Administration (2)] .

Stereochemistry:Propafenone hydrochloride tablets are a racemic mixture. The R- and S-enantiomers of propafenone display stereoselective disposition characteristics. In vitroand in vivostudies have shown that the R-isomer of propafenone is cleared faster than the S-isomer via the 5-hydroxylation pathway (CYP2D6). This results in a higher ratio of S-propafenone to R-propafenone at steady state. Both enantiomers have equivalent potency to block sodium channels; however, the S-enantiomer is a more potent beta-antagonist than the R-enantiomer. Following administration of propafenone hydrochloride immediate-release tablets, the S/R ratio for the area under the plasma concentration-time curve was about 1.7. In addition, no difference in the average values of the S/R ratios is evident between genotypes or over time.

Specific Populations
Patients with Hepatic Impairment:Decreased liver function increases the bioavailability of propafenone. Absolute bioavailability of propafenone hydrochloride immediate-release tablets is inversely related to indocyanine green clearance, reaching 60% to 70% at clearances of 7 mL/min and below. Protein binding decreases to about 88% in patients with severe hepatic dysfunction. The clearance of propafenone is reduced and the elimination half-life increased in patients with significant hepatic dysfunction [see Warnings and Precautions (5.9)] .

13 NONCLINICAL TOXICOLOGY

13.1 Carcinogenesis, Mutagenesis, Impairment of Fertility

Lifetime maximally tolerated oral dose studies in mice (up to 360 mg/kg/day, approximately twice the MRHD on a mg/m^2basis) and rats (up to 270 mg/kg/day, approximately 3 times the MRHD on a mg/m^2basis) provided no evidence of a carcinogenic potential for propafenone.

Propafenone was not mutagenic in the Ames (salmonella) test and the in vivomouse dominant lethal test. Propafenone was not clastogenic in the human lymphocyte chromosome aberration assay in vitro, the rat and Chinese hamster micronucleus tests, and other in vivotests for chromosomal aberrations in rat bone marrow and Chinese hamster bone marrow and spermatogonia.

Propafenone, administered intravenously, has been shown to decrease spermatogenesis at lethal doses in rabbits (≥3.5 mg/kg/day) or at near-lethal dose levels in monkeys and dogs (≤5 mg/kg/day); doses were less than the MRHD on a mg/m^2basis. These effects were reversible and did not impair fertility in rabbits at an intravenous dose of 3.5 mg/kg/day (a spermatogenesis-impairing dose). Effects on spermatogenesis were not found when propafenone was administered to rats either orally or intravenously up to 360 mg/kg/day or 6 mg/kg/day, respectively, or in dogs at oral doses up to 240 mg/kg/day (up to approximately 4 or 9 times the MRHD on the mg/m^2basis in rats and dogs, respectively). Treatment of male rabbits for 10 weeks prior to mating at an oral dose of 120 mg/kg/day (approximately 2 times the MRHD on a mg/m2 basis) did not result in evidence of impaired fertility. Nor was there evidence of impaired fertility when propafenone was administered orally to male and female rats at dose levels up to 270 mg/kg/day (approximately 3 times the MRHD on a mg/m^2basis) for 10 weeks (males) or 2 weeks (females) prior to mating through mating.

13.2 Animal Toxicology and/or Pharmacology

Renal changes have been observed in the rat following 6 months of oral administration of propafenone hydrochloride at doses of 180 and 360 mg/kg/day (about 2 and 4 times, respectively, the MRHD on a mg/m^2basis). Both inflammatory and non-inflammatory changes in the renal tubules, with accompanying interstitial nephritis, were observed. These changes were reversible, as they were not found in rats allowed to recover for 6 weeks. Fatty degenerative changes of the liver were found in rats following longer durations of administration of propafenone hydrochloride at a dose of 270 mg/kg/day (about 3 times the MRHD on a mg/m^2basis). There were no renal or hepatic changes at 90 mg/kg/day (equivalent to the MRHD on a mg/m^2basis).

14 CLINICAL STUDIES

In 2 randomized, crossover, placebo-controlled, double-blind trials of 60 to 90 days’ duration in subjects with PAF or PSVT, propafenone reduced the rate of both arrhythmias, as shown in Table 3.

Table 3. Reduction of Arrhythmias in Subjects with Paroxysmal Atrial Fibrillation/Flutter or Paroxysmal Supraventricular Tachycardia

 | Trial 1 |  | Trial 2
 | Propafenone | Placebo | Propafenone | Placebo
PAF; Percent attack free; Median time to first recurrence | n = 30; 53%; >98 days | n = 30; 13%; 8 days | n = 9; 67%; 62 days | n = 9; 22%; 5 days
PSVT; Percent attack free; Median time to first recurrence | n = 45; 47%; >98 days | n = 45; 16%; 12 days | n = 15; 38%; 31 days | n = 15; 7%; 8 days

The patient population in the above trials was 50% male with a mean age of 57.3 years. Fifty percent of the subjects had a diagnosis of PAF and 50% had PSVT. Eighty percent of the subjects received 600 mg per day propafenone. No subject died in the above 2 trials.

In U.S. long-term safety trials, 474 subjects (mean age: 57.4 ± 14.5 years) with supraventricular arrhythmias [195 with PAF, 274 with PSVT, and 5 with both PAF and PSVT] were treated up to 5 years (mean: 14.4 months) with propafenone. Fourteen of the subjects died. When this mortality rate was compared with the rate in a similar patient population (n = 194 subjects; mean age: 43.0 ± 16.8 years) studied in an arrhythmia clinic, there was no age-adjusted difference in mortality. This comparison was not, however, a randomized trial and the 95% confidence interval around the comparison was large, such that neither a significant adverse or favorable effect could be ruled out.

16 HOW SUPPLIED/STORAGE AND HANDLING

Propafenone Hydrochloride Tablets USP are supplied as:

300 mg – White, biconvex, round, film-coated tablets debossed with “ANI” over “232” and scored on one side and plain on the other side.

- NDC 72162-1753-1: 100 Tablets in a BOTTLE.

Storage:Store at 20° to 25°C (68° to 77°F); [see USP Controlled Room Temperature]. Dispense in a tight, light-resistant container.

Repackaged/Relabeled by:
Bryant Ranch Prepack
Burbank, CA 91504

17 PATIENT COUNSELING INFORMATION

Advise the patient to read the FDA-approved patient labeling (Patient Information).

- Instruct patients to notify their healthcare providers of any change in over-the-counter, prescription, and supplement use.
- Instruct patients to report symptoms that may be associated with altered electrolyte balance, such as excessive or prolonged diarrhea, sweating, vomiting, or loss of appetite or thirst.
- Instruct patients not to double the next dose if a dose is missed. The next dose should be taken at the usual time.

Manufactured by:
ANI Pharmaceuticals, Inc.
Baudette, MN 56623

Patient Information

Propafenone Hydrochloride Tablets USP

What are propafenone hydrochloride tablets?

Propafenone hydrochloride tablets are a prescription medicine that is used:

- in certain people who have ventricular heart rhythm disorders
- to increase the amount of time between having symptoms of heart rhythm disorders called atrial fibrillation (AF) or paroxysmal supraventricular tachycardia (PSVT)

It is not known if propafenone hydrochloride tablets are safe and effective in children.

Who should not take propafenone hydrochloride tablets?

Do not take propafenone hydrochloride tablets if you have:

- heart failure (weak heart)
- had a recent heart attack
- a heart rate that is too slow, and you do not have a pacemaker
- a heart condition called Brugada Syndrome
- very low blood pressure
- certain breathing problems that make you short of breath or wheeze
- certain abnormal body salt (electrolyte) levels in your blood

Talk to your doctor before taking propafenone hydrochloride tablets if you think you have any of the conditions listed above.

What should I tell my doctor before taking propafenone hydrochloride tablets?

Before you take propafenone hydrochloride tablets, tell your doctor if you:

- have liver or kidney problems
- have breathing problems
- have symptoms including diarrhea, sweating, vomiting, or loss of appetite or thirst that are severe. These symptoms may be a sign of abnormal electrolyte levels in your blood.
- have myasthenia gravis
- have lupus erythematosus
- have been told you have or had an abnormal blood test called Antinuclear Antibody Test or ANA Test
- have any other medical conditions
- are pregnant or plan to become pregnant.
- are breastfeeding or plan to breastfeed. Propafenone hydrochloride tablets can pass into your milk. You and your doctor should discuss the best way to feed your baby during this time.

Tell your doctor about all the medicines you take, including prescription and over-the-counter medicines, vitamins, and herbal supplements. Propafenone hydrochloride tablets and certain other medicines can affect (interact with) each other and cause serious side effects. You can ask your pharmacist for a list of medicines that interact with propafenone hydrochloride tablets.

Know the medicines you take. Keep a list of them to show your doctor and pharmacist when you get a new medicine.

How should I take propafenone hydrochloride tablets?

- Take propafenone hydrochloride tablets exactly as prescribed. Your doctor will tell you how many tablets to take and how often to take them.
- To help reduce the chance of certain side effects, your doctor may start you with a low dose of propafenone hydrochloride tablets, and then slowly increase the dose.
- You should not drink grapefruit juice during treatment with propafenone hydrochloride tablets.
- If you miss a dose of propafenone hydrochloride tablets, take your next dose at the usual time. Do not take 2 doses at the same time.
- If you take too much propafenone hydrochloride tablets, call your doctor or go to the nearest hospital emergency room right away.
- Call your doctor if your heart problems get worse.

What are possible side effects of propafenone hydrochloride tablets?

Propafenone hydrochloride tablets can cause serious side effects including:

- New or worsened abnormal heart beats that can cause sudden death or be life-threatening.Your doctor may do an electrocardiogram (ECG or EKG) before and during treatment to check your heart for these problems.
- New or worsened heart failure. Tell your doctor about any changes in your heart symptoms, including:
  - any new or increased swelling in your arms or legs
  - trouble breathing
  - sudden weight gain
- Effects on pacemaker function.Propafenone hydrochloride tablets may affect how an implanted pacemaker or defibrillator works. Your doctor should check how your pacemaker or defibrillator is working during and after treatment with propafenone hydrochloride tablets. They may need to be re-programmed.
- Very low white blood cell levels in your blood (agranulocytosis).Your bone marrow may not produce enough of a certain type of white blood cells called neutrophils. If this happens, you are more likely to get infections. Tell your doctor right away if you have any of these symptoms, especially during the first 3 months of treatment:
  - fever
  - sore throat
  - chills
- Worsening of myasthenia gravis in people who already have this condition.Tell your doctor about any change in your symptoms.
- Propafenone hydrochloride tablets may cause lower sperm counts in men.This could affect the ability to father a child. Talk to your doctor if this is a concern for you.

Common side effects of propafenone hydrochloride tablets include:

- unusual taste
- nausea
- vomiting
- dizziness
- constipation
- headache
- tiredness
- irregular heartbeats

Tell your doctor if you have any side effect that bothers you or that does not go away.

These are not all the possible side effects of propafenone hydrochloride tablets. For more information, ask your doctor or pharmacist.

Call your doctor for medical advice about side effects. You may report side effects to FDA at 1-800-FDA-1088.

How should I store propafenone hydrochloride tablets?

- Store propafenone hydrochloride tablets at room temperature between 68°F to 77°F (20°C to 25°C).
- Keep the bottle tightly closed.

Keep propafenone hydrochloride tablets and all medicines out of the reach of children.

General information about propafenone hydrochloride tablets

Medicines are sometimes prescribed for purposes other than those listed in a Patient Information Leaflet. Do not use propafenone hydrochloride tablets for a condition for which it was not prescribed. Do not give propafenone hydrochloride tablets to other people, even if they have the same symptoms you have. It may harm them.

If you would like more information, talk with your doctor. You can ask your doctor or pharmacist for information about propafenone hydrochloride tablets that is written for health professionals. For more information about propafenone hydrochloride tablets, call 1-800-308-6755.

What are the ingredients in propafenone hydrochloride tablets?

Active ingredient: Propafenone hydrochloride

Inactive ingredients: Corn starch, croscarmellose sodium, hypromellose, maltodextrin, magnesium stearate, microcrystalline cellulose, polydextrose, polyethylene glycol, povidone, silicon dioxide colloidal, titanium dioxide, and triacetin.

This Patient Information has been approved by the U.S. Food and Drug Administration.

Manufactured by:
ANI Pharmaceuticals, Inc.
Baudette, MN 56623

9691 Rev 11/18

PACKAGE LABEL

Propafenone Hydrochloride 300mg Tablets